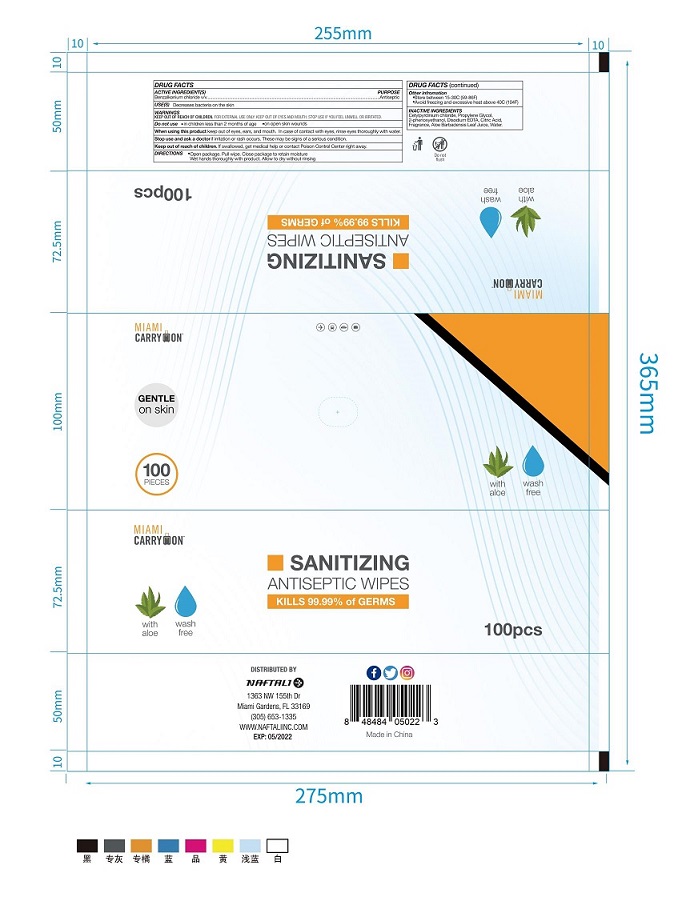 DRUG LABEL: antiseptic wipes
NDC: 77412-012 | Form: CLOTH
Manufacturer: Shandong Liaocheng Chaoyue Daily Necessities Co., Ltd.
Category: otc | Type: HUMAN OTC DRUG LABEL
Date: 20210205

ACTIVE INGREDIENTS: BENZALKONIUM CHLORIDE 0.13 1/100 1
INACTIVE INGREDIENTS: WATER; ALOE VERA LEAF 0.01 1/100 1; ANHYDROUS CITRIC ACID 0.001 1/100 1; CETYLPYRIDINIUM CHLORIDE ANHYDROUS 0.02 1/100 1; PROPYLENE GLYCOL 0.1 1/100 1; PHENOXYETHANOL 0.02 1/100 1; EDETATE DISODIUM ANHYDROUS 0.001 1/100 1

sanitizing antiseptic wipes

This is a hand sanitizer manufactured according to the Temporary Policy for Preparation of Certain Alcohol-Based Hand Sanitizer Products During the Public Health Emergency (CoViD-19); Guidance for Industry.

The hand sanitizer is manufactured using only the following United States Pharmacopoeia (USP) grade ingredients in the preparation of the product (percentage in final product formulation) consistent with World Health Organization (WHO) recommendations:

1. BENZALKONIUM CHLORIDE (0.13% v/v).
2. CETYLPYRIDINIUM CHLORIDE(0.02% v/v).
3. PROPYLENE GLYCOL(0.1% v/v).
4. PHENOXYETHANOL(0.02% v/v).
5. EDETATE DISODIUM(0.001% v/v).
6. ANHYDROUS CITRIC ACID(0.001% v/v).
7. ALOE VERA LEAF(0.01% v/v).
8. Sterile distilled water or boiled cold water.

The firm does not add other active or inactive ingredients. Different or additional ingredients may impact the quality and potency of the product.

Active Ingredient(s)

BENZALKONIUM CHLORIDE 0.13% v/v.

Purpose

Antiseptic

Use

Decreases bacteria on the skin

Warnings

For external use only. Flammable. Keep away from heat or flame

Do not use

- in children less than 2 months of age
- on open skin wounds

When using this product keep out of eyes, ears, and mouth. In case of contact with eyes, rinse eyes thoroughly with water.
Stop use and ask a doctor if irritation or rash occurs. These may be signs of a serious condition.
Keep out of reach of children. If swallowed, get medical help or contact a Poison Control Center right away.

Stop use and ask a doctor if irritation or rash occurs. These may be signs of a serious condition.

Keep out of reach of children. If swallowed, get medical help or contact a Poison Control Center right away.

Directions

- Open package. Pull wipe. Close package to remain moisture
- Wet hands thoroughly with product. Allow to dry without rinsing

Other information

- Store between 15-30C (59-86F)
- Avoid freezing and excessive heat above 40C (104F)

Inactive ingredients

CETYLPYRIDINIUM CHLORIDE(0.02% v/v).
PROPYLENE GLYCOL(0.1% v/v).
PHENOXYETHANOL(0.02% v/v).
EDETATE DISODIUM(0.001% v/v).
ANHYDROUS CITRIC ACID(0.001% v/v).
ALOE VERA LEAF(0.01% v/v).
FRAGRANCE
WATER

Package Label - Principal Display Panel

77412-012-01